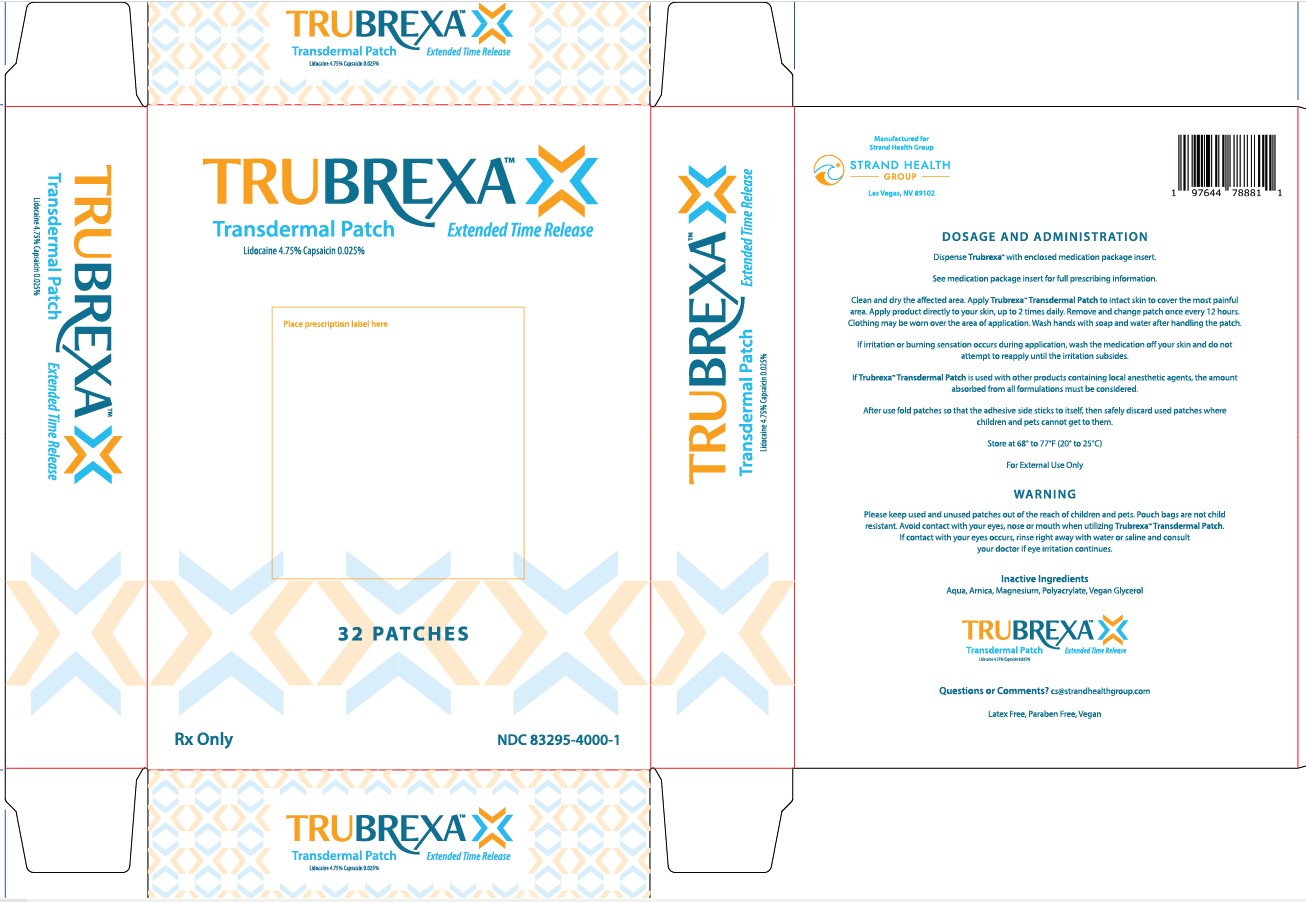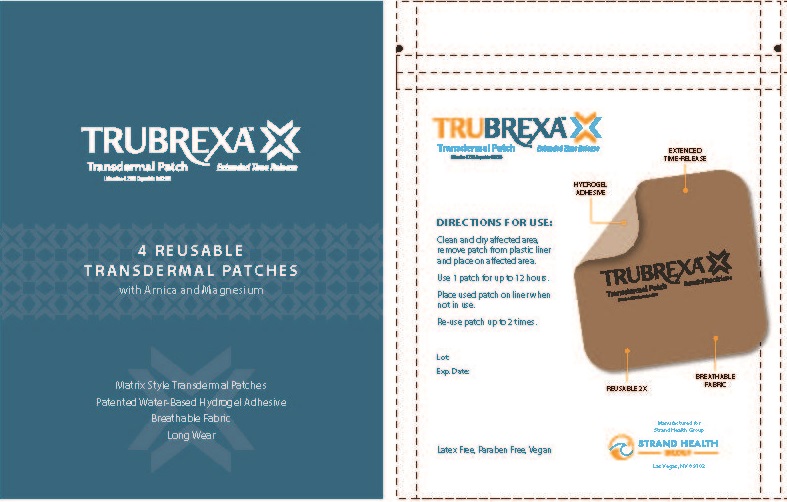 DRUG LABEL: Trubrexa
NDC: 83295-4000 | Form: PATCH
Manufacturer: Strand Health Group
Category: prescription | Type: HUMAN PRESCRIPTION DRUG LABEL
Date: 20251218

ACTIVE INGREDIENTS: CAPSAICIN 0.00025 g/1 g; LIDOCAINE 0.0475 g/1 g
INACTIVE INGREDIENTS: GLYCERIN; ARNICA MONTANA FLOWER; POLYACRYLIC ACID (250000 MW); MAGNESIUM; WATER

Trubrexa Transdermal Patch

TrubrexaTM Transdermal Patch

Extended Time Release

Lidocaine 4.75%

Capsaicin 0.025%

Rx Only

1. INDICATIONS & USAGE

TrubrexaTM Transdermal Patch is indicated in adults over the age of 12 years old for the treatment of acute and chronic pain in muscles and joints associated with muscle soreness, strains, sprains, arthritis, simple backache, muscle stiffness, and more.

2. DOSAGE & ADMINISTRATION

2.1 Important Dosage and Administration Instructions

- Unintended exposure to capsaicin can cause severe irritation of the eyes, mucous membranes, respiratory tract, and skin in healthcare providers and others.
- Because unintended exposure to capsaicin can cause severe irritation of eyes, mucous membranes, respiratory tract, and skin, when administering TrubrexaTM Transdermal Patch it is important to follow these procedures:
  - Keep TrubrexaTM Transdermal Patch in the sealed pouch until immediately before use.
  - Use TrubrexaTM Transdermal Patch only on dry, intact (unbroken) skin.
  - During administration, avoid unnecessary contact with any items in the room, including items that the patient may later have contact with, such as horizontal surfaces and bedsheets.
  - Immediately after use, clean all areas of skin that had contact with TrubrexaTM Transdermal Patch.
  - Ensure all used and unused pieces TrubrexaTM Transdermal Patch are properly disposed of.

2.2 Dosing and Instructions for Use

- Tear open pouch bag and remove one patch. Place remaining patches back in pouch bag and seal the pouch bag closed.
- Peel the clear plastic film away and apply TrubrexaTM Transdermal Patch to intact skin to cover the most painful area. Apply one patch per day for up to 12 hours within a 24 hour period (12 on, 12 off). One single TrubrexaTM Transdermal Patch may be used twice per day. To re-use after first application, place the clear plastic film back on to medicated hydrogel pad.
- Clothing may be worn over the area of application.
- Wash hands with soap and water after handling the patch.
- If irritation or a burning sensation occurs during application, remove the patch and do not reapply until the irritation subsides.
- When TrubrexaTM Transdermal Patch is used concomitantly with other products containing local anesthetic agents, the amount absorbed from all formulations must be considered.

3. DOSAGE FORMS & STRENGTHS

TrubrexaTM Transdermal Patch contains 4.75% lidocaine and 0.025% capsaicin. Each patch is 2 in x 2 in (5.08 cm x 5.08 cm) and consists of an adhesive side containing the active/inactive ingredients and an outer surface backing layer. The adhesive side is covered with a removable, clear, unprinted, plastic film. The outer surface of the backing layer is imprinted with the TrubrexaTM Transdermal Patch logo.

4. CONTRAINDICATIONS

TrubrexaTM Transdermal Patch is contraindicated in patients with a known history of sensitivity to local anesthetics of the amide type, or to any other component of the product.

5. WARNINGS, PRECAUTIONS & ADVERSE REACTIONS

5.1 Risk of Methemoglobinemia

Inform patients that use of local anesthetics may cause methemoglobinemia, a serious condition that must be treated promptly. Advise patients or caregivers to stop use and seek immediate medical attention if they or someone in their care experience the following signs or symptoms: pale, gray, or blue colored skin (cyanosis); headache; rapid heart rate; shortness of breath; fatigue; or lightheadedness.

Cases of methemoglobinemia have been reported in association with local anesthetic use. Although all patients are at risk for methemoglobinemia, patients with glucose-6-phosphate dehydrogenase deficiency, congenital or idiopathic methemoglobinemia, cardiac or pulmonary compromise, infants under 6 months of age, and concurrent exposure to oxidizing agents or their metabolites are more susceptible to developing clinical manifestations of the condition. If local anesthetics must be used in these patients, close monitoring for symptoms and signs of methemoglobinemia is recommended.

Signs of methemoglobinemia may occur immediately or may be delayed some hours after exposure and are characterized by cyanotic skin discoloration and/or abnormal coloration of the blood. Methemoglobin levels may continue to rise; therefore, immediate treatment is required to avert more serious central nervous system and cardiovascular adverse effects, including seizures, coma, arrhythmias, and death. Discontinue TrubrexaTM Transdermal Patch and any other oxidizing agents. Depending on the severity of the signs and symptoms, patients may respond to supportive care, i.e., oxygen therapy, hydration, etc. A more severe clinical presentation may require treatment with methylene blue, exchange transfusion, or hyperbaric oxygen.

5.2 Excessive Dosing

Excessive dosing by applying TrubrexaTM Transdermal Patch to larger areas or for longer than the recommended wearing time could result in increased absorption of lidocaine and capsaicin and high blood concentrations. Lidocaine toxicity could b e expected at lidocaine blood concentrations above 5 mcg/mL. The blood concentration of lidocaine is determined by the rate of systemic absorption and elimination. Longer duration of application, application of more than the recommended number of patches, smaller patients, or impaired elimination may all contribute to increasing the blood concentration of lidocaine and capsaicin.

5.3 Severe Irritation with Unintended Capsaicin Exposure

Unintended exposure to capsaicin can cause severe irritation of eyes, mucous membranes, respiratory tract, and skin.

Eye and Mucous Membrane Exposure

- Do not apply TrubrexaTM Transdermal Patch to the face, eyes, mouth, nose, or scalp to avoid risk of exposure to eyes or mucous membranes.
- Accidental exposure to the eyes and mucous membranes can occur from touching TrubrexaTM Transdermal Patch or items exposed to capsaicin, then touching the eyes and mucous membranes.
- If irritation of eyes or mucous membranes occurs, remove the affected individual from the vicinity of TrubrexaTM Transdermal Patch and flush eyes and mucous membranes with cool water.

Respiratory Tract Exposure

- Inhalation of airborne capsaicin can result in coughing or sneezing. If irritation of airways occurs, remove the affected individual from the vicinity of TrubrexaTM Transdermal Patch. Provide supportive medical care if shortness of breath develops.

Skin Exposure

- Thoroughly clean all areas that had contact with TrubrexaTM Transdermal Patch and properly dispose of all patch components.

5.4 Application-Associated Pain

During or immediately after treatment with TrubrexaTM Transdermal Patch, the skin at the site of application may develop blisters, bruising, burning sensation, depigmentation, dermatitis, discoloration, edema, erythema, exfoliation, irritation, papules, petechia, pruritus, vesicles, or may be the locus of abnormal sensation. These reactions are generally mild and transient, resolving spontaneously within a few minutes to hours.

5.5 Increase in Blood Pressure

Patient with unstable or poorly controlled hypertension, or a recent history of cardiovascular or cerebrovascular events, may be at increased risk of adverse cardiovascular effects. Consider these factors prior to initiating TrubrexaTM Transdermal Patch treatment. Monitor blood pressure periodically during and following the treatment procedure and provide adequate support for treatment-related pain.

5.6 Sensory Function

Decreases in sensory functions are generally minor and temporary (including to thermal and other harmful stimuli). All patients with pre-existing sensory deficits should be clinically assessed for signs of sensory deterioration or loss prior to each prescription of TrubrexaTM Transdermal Patch. If sensory deterioration or loss is detected or pre-existing sensory deficit worsens, continued use of TrubrexaTM Transdermal Patch treatment should be reconsidered.

5.7 Precautions

Allergic Reactions

Allergic and anaphylactoid reactions associated with lidocaine can occur. They are characterized by angioedema, bronchospasm, dermatitis, dyspnea, hypersensitivity, laryngospasm, pruritus, chock, and urticaria. If they occur, they should be managed by conventional means. Patients allergic to para-aminobenzoic acid derivates (procaine, tetracaine, benzocaine, etc.) have not shown cross-sensitivity to lidocaine. However, TrubrexaTM Transdermal Patch should be used with caution in patients with a history of drug sensitivities, especially if the etiologic agent is uncertain.

External Heat Sources

Placement of external heat sources, such as heating pads or electric blankets, over TrubrexaTM Transdermal Patch is not recommended.

Eye Exposure

The contact of TrubrexaTM Transdermal Patch with eyes should be avoided based on finding from previous studies with use of similar products. If eye contact occurs, immediately wash out the eye with water and saline and protect the eye until sensation returns.

Hepatic Disease

Patients with severe hepatic disease are at greater risk of developing toxic blood concentrations of lidocaine, because of their inability to metabolize lidocaine normally.

Non-Intact Skin

TrubrexaTM Transdermal Patch is only recommended for use on intact skin. Application to broken or inflamed skin may result in increased irritation and/or increased absorption of ingredients.

5.8 Other Adverse Events

Due to the nature and limitation of spontaneous reports in postmarketing surveillance, causality has not been established for additional reported adverse events including: asthenia, confusion, disorientation, dizziness, headache, hyperesthesia, hypoesthesia, lightheadedness, metallic taste, nausea, nervousness, pain exacerbated, paresthesia, somnolence, taste alteration, vomiting, visual disturbances such as blurred vision, flushing, tinnitus, and tremor.

5.9 Systemic (Dose-Related) Reactions

Systemic adverse reactions following appropriate use of TrubrexaTM Transdermal Patch are unlikely due to the small dose absorbed. Systemic adverse effects of lidocaine are similar in nature to those observed with other amide local anesthetic agents, including CNS excitation and/or depression (light headedness, nervousness, apprehension, euphoria, confusion, dizziness, drowsiness, tinnitus, blurred or double vision, vomiting, sensations of heat, cold, or numbness, twitching tremors, convulsions, unconsciousness, respiratory depression, and arrest). Excitatory CNS reactions may be brief or not occur at all, in which case the first manifestations may include bradycardia, hypotension, and cardiovascular collapse leading to arrest.

6. DRUG INTERACTIONS

Antiarrhythmic Drugs

TrubrexaTM Transdermal Patch should be used with caution in patients receiving Class I antiarrhythmic drugs (such as tocainide and mexiletine) since the toxic effects are additive and potentially synergistic.

Local Anesthetics

When TrubrexaTM Transdermal Patch is used concomitantly with other products containing local anesthetic agents, the amount absorbed from all formulations must be considered.

Drugs That May Cause Methemoglobinemia

Patients who are administered local anesthetics are at increased risk of developing methemoglobinemia when concurrently exposed to the following drugs, which could include other local anesthetics:

Nitrates/Nitrites (nitric oxide, nitroglycerin, nitroprusside, nitrous oxide)

Local anesthetics (benzocaine, bupivacaine, lidocaine, prilocaine, procaine, tetracaine)

Antineoplastic Agents (cyclophosphamide, flutamide, hydroxyurea, ifosfamide, rasburicase)

Antibiotics (dapsone, nitrofurantoin, para-aminosalicylic acid, sulfonamides)

Antimalarials (chloroquine, primaquine)

Anticonvulsants (Phenobarbital, phenytoin, sodium valproate)

Other Drugs (acetaminophen, metoclopramide, quinine, sulfasalazine)

7. USE IN SPECIFIC POPULATIONS

7.1 Pregnancy

TrubrexaTM Transdermal Patch has not been studied in pregnancy. Maternal use is not expected to result in fetal exposure. Animal studies have shown no adverse effects when lidocaine and capsaicin are administered and absorbed. There are, however, no adequate and well-controlled studies in pregnant women. Because animal reproduction studies are not always predictive of human response, TrubrexaTM Transdermal Patch should only be used during pregnancy if clearly needed or advised by a healthcare professional. All pregnancies have a background risk of birth defect, loss, or other adverse outcomes.

7.2 Lactation

TrubrexaTM Transdermal Patch has not been studied in nursing mothers. Lidocaine is excreted in human milk, and the milk:plasma ration of lidocaine is 0.4. Capsaicin is negligibly absorbed systemically by the mother following topical administration of TrubrexaTM Transdermal Patch. Caution should be exercised when TrubrexaTM Transdermal Patch is administered to a nursing woman. The developmental and health benefits of breastfeeding should be considered along with the mother’s clinical need for TrubrexaTM Transdermal Patch and any potential adverse effects on the breastfed infant.

7.3 Pediatric Use

Safety and effectiveness in pediatric patients under the age of 12 have not been studied or established.

7.4 Geriatric Use

Safety and effectiveness are similar in geriatric patients and younger patients. No dose adjustments are required in geriatric patients.

8. OVERDOSAGE

Lidocaine overdose from cutaneous absorption is rare but could occur. If there is any suspicion of lidocaine overdose, drug blood concentration should be checked. The management of overdose includes close monitoring, supportive care, and symptomatic treatment. Dialysis is of negligible value in the treatment of acute overdose with lidocaine. In the absence of massive topical overdose or oral ingestion, evaluation of symptoms of toxicity should include consideration of other etiologies for the clinical effects, or overdosage from other sources of lidocaine or other local anesthetics. There is no specific antidote for overdose with capsaicin. In case of suspected overdose, remove TrubrexaTM Transdermal Patch and gently wash the area with soap and water. Use supportive measures and treat symptoms as clinically warranted.

9. DESCRIPTION

TrubrexaTM Transdermal Patch is comprised of an adhesive material containing 4.75% lidocaine and 0.025% capsaicin. Each patch is 2 in x 2 in (5.08 cm x 5.08 cm) and consists of an adhesive side containing the active/inactive ingredients and an outer surface backing layer with breathable fabric. The adhesive side is covered with a removable, clear, unprinted, plastic film. The outer surface of the backing layer is imprinted with the TrubrexaTM Transdermal Patch logo. 4 patches are included in each pouch bag. The inactive ingredients include: Arnica, Magnesium, Polyacrylate, Vegan Glycerol, and Water. TrubrexaTM Transdermal Patch is Latex Free, Paraben Free, and Vegan.

10. CLINICAL PHARMACOLOGY

10.1 Pharmacodynamics

Lidocaine is chemically designated as acetamide, 2-(diethylamino)-N-(2,6-dimethylphenyl), has an octanol:water partition ratio of 43 at pH 7.4. Capsaicin is soluble in alcohol, acetone, and ethyl acetate and very slightly soluble in water. Lidocaine is an amide-type local anesthetic agent and is suggested to stabilize neuronal membranes by inhibiting the ionic fluxes required for the initiation and conduction of impulses. The penetration of lidocaine into intact skin after application of TrubrexaTM Transdermal Patch is sufficient to produce an analgesic effect, but less than the amount necessary to produce a complete sensory block. Capsaicin is an agonist for the transient receptor potential vanilloid 1 receptor (TRPV1), which is an ion channel-receptor complex expressed on nociceptive nerve fibers in the skin. Topical administration of capsaicin causes an initial enhanced stimulation of the TRPV1-expressing cutaneous nociceptors that may be associated with painful sensations. This is followed by pain relief thought to be mediated by a reduction in TRPV1-expressing nociceptive nerve endings.

10.2 Pharmacokinetics

The amount of lidocaine and capsaicin systemically absorbed from TrubrexaTM Transdermal Patch is directly related to both the duration of application and the surface area over which it is applied. Systemic exposure decreases upon removal of TrubrexaTM Transdermal Patch. Lidocaine crosses the placental and blood brain barriers, presumably by passive diffusion. It is not known if lidocaine is metabolized in the skin. Lidocaine is metabolized rapidly by the liver to a number of metabolites, including monoethylglycinexylidide (MEGX) and glycinexylidide (GX), both of which have pharmacologic activity similar to, but less potent than that of lidocaine. Lidocaine and its metabolites are excreted by the kidneys.

11. NONCLINICAL TOXICOLOGY

11.1 Carcinogenesis, Mutagenesis, Impairment of Fertility

Carcinogenesis

A minor metabolite, 2,6-xylidine, has been found to be carcinogenic in rats. The blood concentration of this metabolite is negligible following application of TrubrexaTM Transdermal Patch.

Mutagenesis

Lidocaine HCl is not mutagenic in Salmonella/mammalian microsome test nor clastogenic in chromosome aberration assay with human lymphocytes and mouse micronucleus test.

Impairment of Fertility

The effect of TrubrexaTM Transdermal Patch on fertility has not been studied.

12. HOW SUPPLIED / STORAGE & HANDLING

12.1 How Supplied

TrubrexaTM Transdermal Patch comes in a sealed pouch bag. Each patch is 2 in x 2 in (5.08 cm x 5.08 cm) and consists of an adhesive side containing the active/inactive ingredients and an outer surface backing layer. The adhesive side is covered with a removable, clear, unprinted, plastic film. The outer surface of the backing layer is imprinted with the TrubrexaTM Transdermal Patch logo.

TrubrexaTM Transdermal Patch is available as a unit box containing 32 patches (8 pouch bags). NDC 83295-4000-1

12.2 Storage

Store unit box between 68o-77o F (20o-25o C). Excursions between 15o-30o C (59o-86o F) are allowed. Keep TrubrexaTM Transdermal Patch in the sealed pouch bags until immediately before use.

12.3 Handling and Disposal

Unintended exposure to capsaicin can cause severe irritation of eyes, skin, respiratory tract, and mucous membranes. Avoid contact with your eyes, nose, or mouth. Keep used and unused patches out of the reach of children and pets. Pouch bags are not child resistant. Wash hands with soap and water after handling the patch. If irritation or a burning sensation occurs during application, remove the patch and do not reapply until the irritation subsides. After use, fold patches so that the adhesive side sticks to itself, then safely discard used patches where children and pets cannot get to them.

13. PATIENT COUNSELING INFORMATION

- Inform patients that accidental exposure to capsaicin from touching TrubrexaTM Transdermal Patch can cause severe irritation of eyes, mucous membranes, respiratory tract, and skin. If this occurs, patient should notify a healthcare professional immediately.
- Inform patients that the treated area may be sensitive to heat (e.g., hot showers/bath, direct sunlight, vigorous exercise) for a few days following treatment.
- Inform patients that as a result of treatment-related increases in pain, small transient increases in blood pressure may occur during and shortly after TrubrexaTM Transdermal Patch treatment and that blood pressure will be monitored during the treatment process. If any cardiovascular event occurs, patient should notify a healthcare professional immediately.

Manufactured for Strand Health Group, Las Vegas, NV 89102, USA.

Copyright © 2023 Strand Health Group, LLC. All Rights Reserved.

For comments or questions, please email cs@strandhealthgroup.com.

NDC 83295-4000-1

TrubrexaTM Transdermal Patch

Extended Time Release

Rx Only

[Trubrexa Logo]